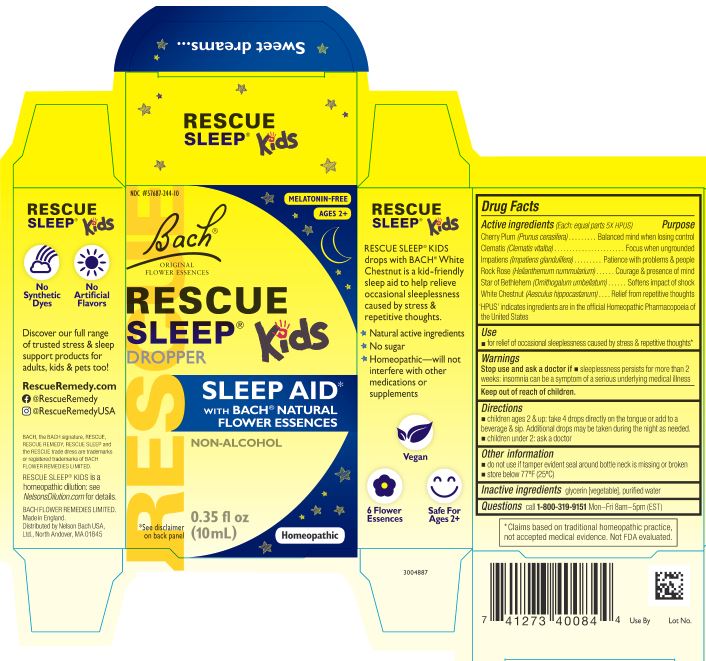 DRUG LABEL: Rescue Sleep Kids
NDC: 57687-244 | Form: SOLUTION
Manufacturer: Nelson Bach USA Limited
Category: homeopathic | Type: HUMAN OTC DRUG LABEL
Date: 20230727

ACTIVE INGREDIENTS: HELIANTHEMUM NUMMULARIUM FLOWER 5 [hp_X]/0.095 mL; CLEMATIS VITALBA FLOWER 5 [hp_X]/0.095 mL; IMPATIENS GLANDULIFERA FLOWER 5 [hp_X]/0.095 mL; PRUNUS CERASIFERA FLOWER 5 [hp_X]/0.095 mL; ORNITHOGALUM UMBELLATUM WHOLE 5 [hp_X]/0.095 mL; AESCULUS HIPPOCASTANUM FLOWER 5 [hp_X]/0.095 mL
INACTIVE INGREDIENTS: GLYCERIN; WATER

Rescue Sleep Kids
Dropper

ACTIVE INGREDIENT

(Each: equal parts 5X HPUS)

Cherry Plum (Prunus cerasifera)

Clematis (Clematis vitalba)

Impatiens (Impatiens glandulifera)

Rock Rose (Helianthemum nummularium)

Star of Bethlehem (Ornithogalum umbellatum)

White Chestnut (Aesculus hippocastanum)

'HPUS' indicates ingredients are in the official Homeopathic Pharmacopoeia of the United States

PURPOSE

Cherry Plum (Prunus cerasifera) - Balanced mind when losing control

Clematis (Clematis vitalba) - Focus when undgrounded

Impatiens (Impatiens glandulifera) - Patience with problems & people

Rock Rose (Helianthemum nummularium) - Courage & presence of mind

Star of Bethlehem (Ornithogalum umbellatum) - Softens impact of shock

White Chestnut (Aesculus hippocastanum) - Relief from repetative thoughts

Use

- for relief of occasional sleeplessness caused by stress and repetitive thoughts

WARNINGS

Stop use and ask a doctor if sleeplessness persists for more than 2 weeks: insomnia can be a symptom of a serius underlying medical illness

Keep out of reach of children.

Directions

- children ages 2 and up: take 4 drops directly on tongue, or add to a beverage and sip. Additional drops may be taken during the night as needed.
- children under 2: ask a doctor

Other information

- do not use if tamper evident seal around bottle neck is missing or broken
- store below 77°F (25°C)

Inactive ingredients

glycerin [vegetable], puriﬁed water

Questions

call 1-800-319-9151 Mon–Fri 8am–5pm (EST)